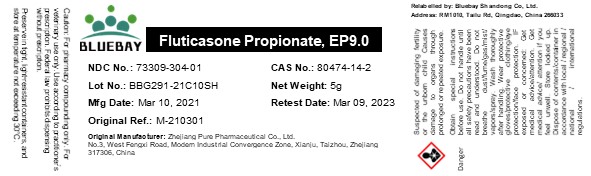 DRUG LABEL: Fluticasone Propionate
NDC: 73309-304 | Form: POWDER
Manufacturer: BLUEBAY SHANDONG CO.,LTD
Category: other | Type: BULK INGREDIENT
Date: 20210621

ACTIVE INGREDIENTS: FLUTICASONE PROPIONATE 1 g/1 g

Fluticasone Propionate